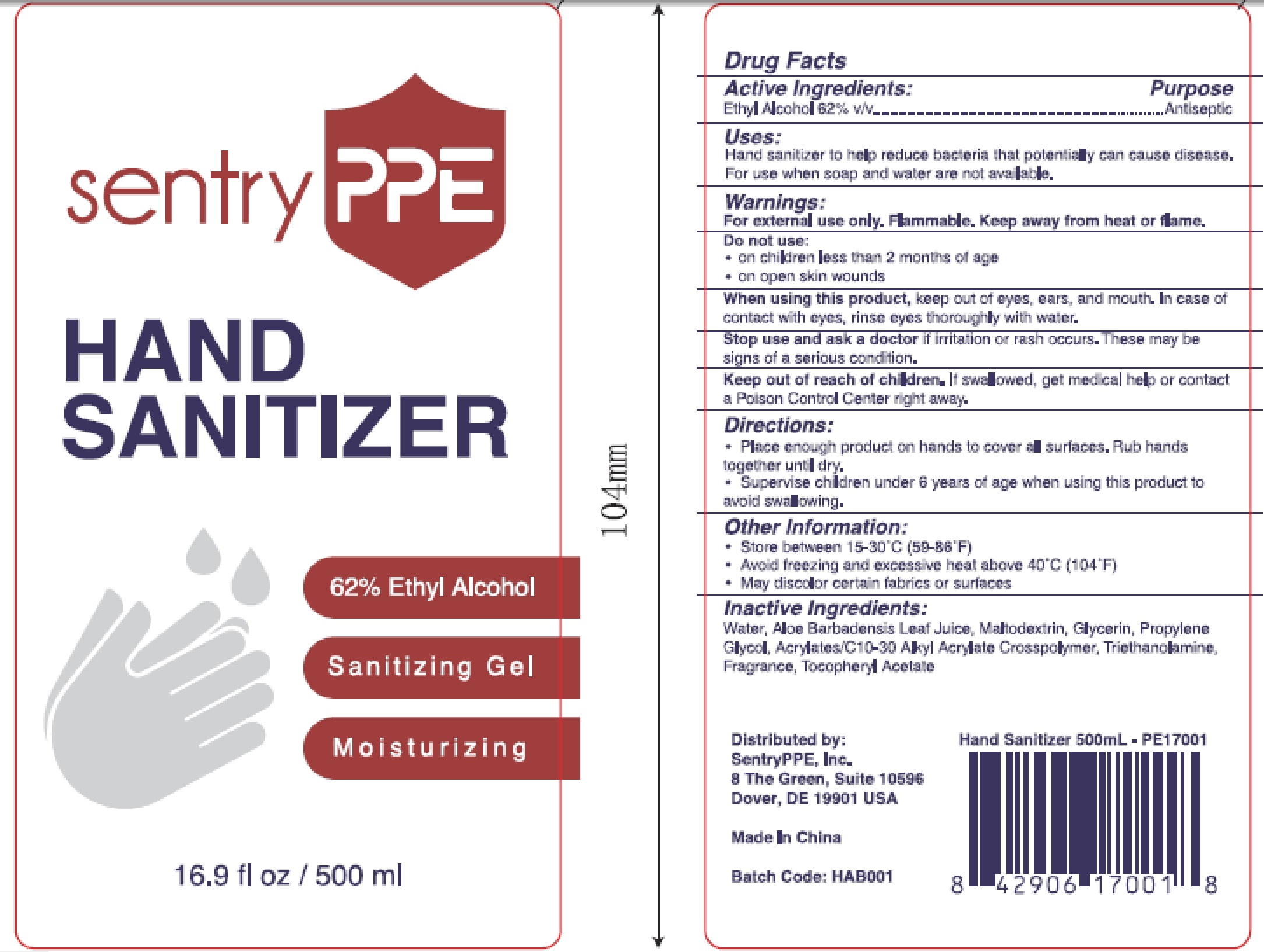 DRUG LABEL: Hand Sanitizer
NDC: 78398-169 | Form: GEL
Manufacturer: SentryPPE, Inc.
Category: otc | Type: HUMAN OTC DRUG LABEL
Date: 20200528

ACTIVE INGREDIENTS: ALCOHOL 62 mL/100 mL
INACTIVE INGREDIENTS: MALTODEXTRIN; PROPYLENE GLYCOL; WATER; ALOE VERA LEAF; GLYCERIN; CARBOMER INTERPOLYMER TYPE A (55000 CPS); TROLAMINE; .ALPHA.-TOCOPHEROL ACETATE

Active Ingredient
Ethyl Alcohol 62% v/v

Purpose
Antiseptic

Uses:

Hand sanitizer to help reduce bacteria that potentially can cause disease.

For use when soap and water not available.

Warnings:

For external use only. Flammable. Keep away from heat or flame.

Do not use:

On children less than 2 months of age

On open skin wounds

When using this product, keep out of eyes, ears, and mouth. In case of contact with eyes, rinse eyes thoroughly with water.

Stop use and ask a doctor if irritation or rash occurs. These may be signs of a serious condition.

Keep out of reach of children. If swallowed, get medical help or contact a Poison Control Center right way.

Directions

Place enough product on hands to cover all surfaces. Rub hands together until dry.

Supervise Children under 6 years of age when using this product to avoid swallowing.

Other Information:

Store between 15-30℃（59-86℉）

Avoid freezing and excessive heat above 40℃(104℉)

May discolor certain fabrics or surfaces.

Inactive Ingredients

Water, Aloe Barbadensis Leaf Juice, Maltodextrin,Glycerin, Propylene Glycol, Acrylates/C1O-30 Alkyl Acrylate Crosspolymer, Triethanoamine, Fragrance, Tocopheryl Acetate.